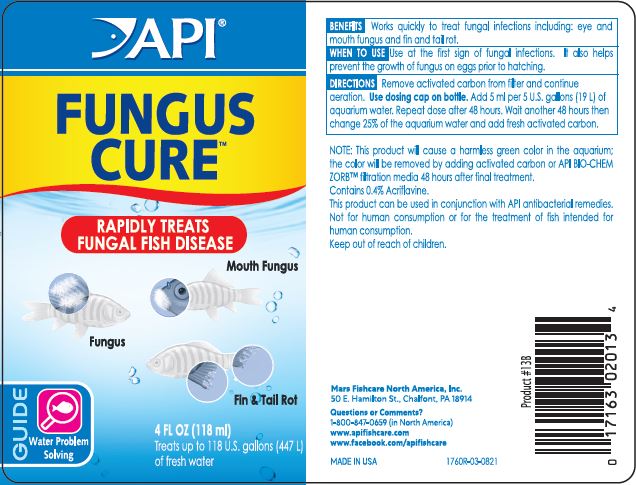 DRUG LABEL: API Fungus Cure
NDC: 17163-108 | Form: LIQUID
Manufacturer: MARS FISHCARE NORTH AMERICA, INC.
Category: animal | Type: OTC ANIMAL DRUG LABEL
Date: 20220207

ACTIVE INGREDIENTS: ACRIFLAVINE 4 mg/1 mL

Drug Label

DESCRIPTION

BENEFITS

Works quickly to treat fungal infections including: eye and mouth fungus and fin and tail rot.

INDICATIONS AND USAGE

WHEN TO USE

Use at the first sign of fungal infections.

It also helps prevent the growth of fungus on eggs prior to hatching.

DIRECTIONS

Remove activated carbon from filter and continue aeration.

Use dosing cap on bottle.

Add 5 ml per 5 U.S. gallons (19 L) of aquarium water.

Repeat dose after 48 hours. Wait another 48 hours then change 25% of the aquarium water and add fresh activated carbon.

RESIDUE WARNING

NOTE: This product will cause a harmless green color in the aquarium: the color will be removed by adding activated carbon or API BIO-CHEM ZORB filtration media 48 hours after final treatment.

This product can be used in conjunction with API antibacterial remedies.

USER SAFETY WARNINGS

Not for human consumption or for the treatment of fish intended for human consumption.

Keep out of reach of children.

ACTIVE INGREDIENT

Contains: 0.4% Acriflavine

Questions or Comments?

1-800-847-0659 (In North America)

www.apifishcare.com

www.facebook.com/apifishcare

PACKAGE LABEL

API

FUNGUS

CURE

Rapidly Treats

Fungal Fish Disease

Mouth Fungus

Fungus

Fin and Tail Rot

GUIDE

Water Problem

Solving

4 FL OZ (118 mL)

Treats up to 118 U.S. Gallons (447 L)

of fresh water